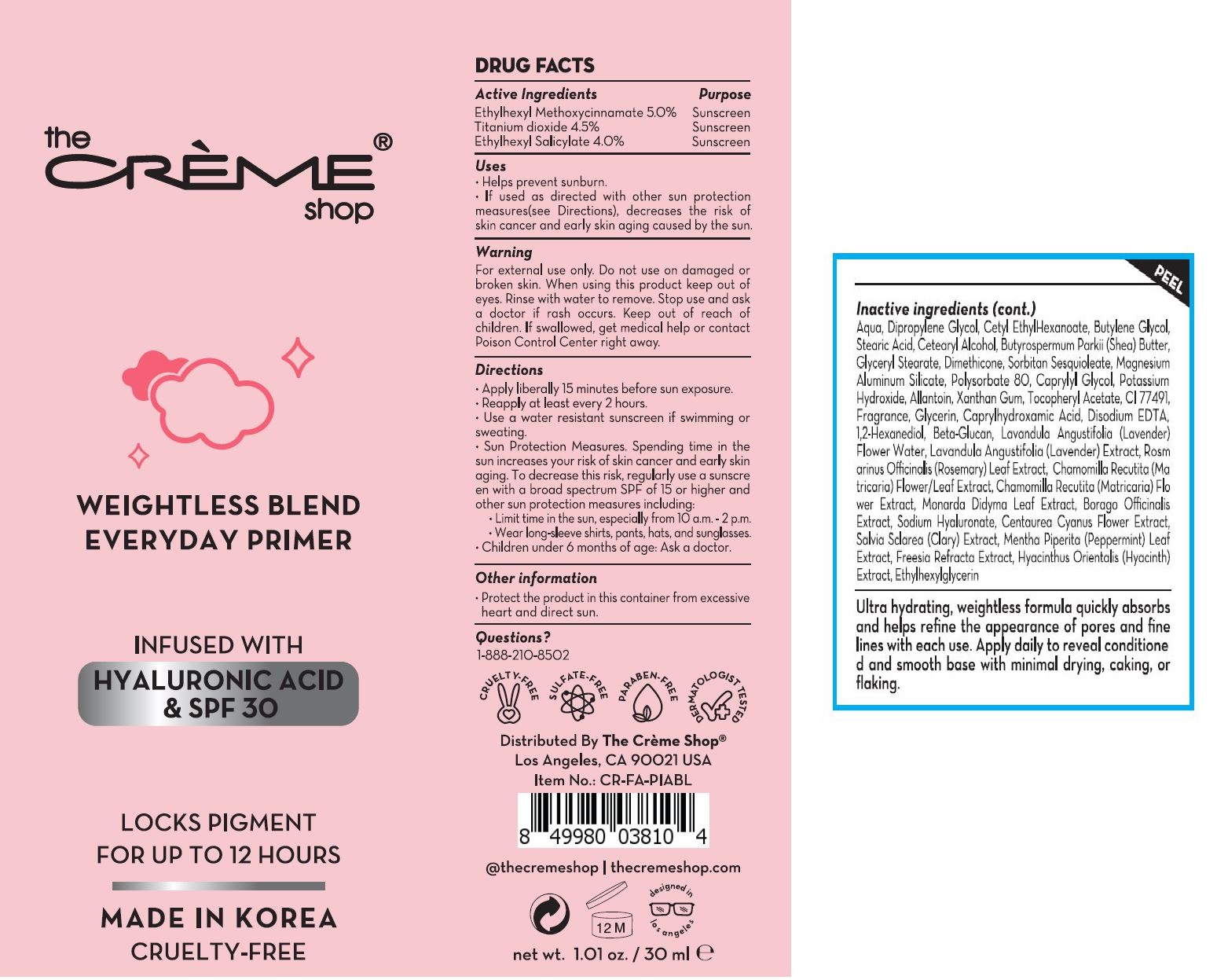 DRUG LABEL: TCS WEIGHTLESS BLEND EVERYDAY PRIMER
NDC: 81677-0001 | Form: CREAM
Manufacturer: Beyond Cosmetics co. , Ltd
Category: otc | Type: HUMAN OTC DRUG LABEL
Date: 20210313

ACTIVE INGREDIENTS: TITANIUM DIOXIDE 4.5 g/100 mL; OCTINOXATE 5 g/100 mL; OCTISALATE 4 g/100 mL
INACTIVE INGREDIENTS: WATER

ACTIVE INGREDIENT

ethylhexyl methoxycinnamate, titanium dioxide, ethylhexyl salicylate

INACTIVE INGREDIENT

water, dpropylene glycol, butylene glycol, etc

PURPOSE

helps prevent sunburn

KEEP OUT OF REACH OF CHILDREN

WARNING

for external use only

do not use on damaged or broken skin

USES

for external use only

INDICATION & USAGE SECTION

apply liberally 15 minutes before sun exposure

reapply at least every 2 hours